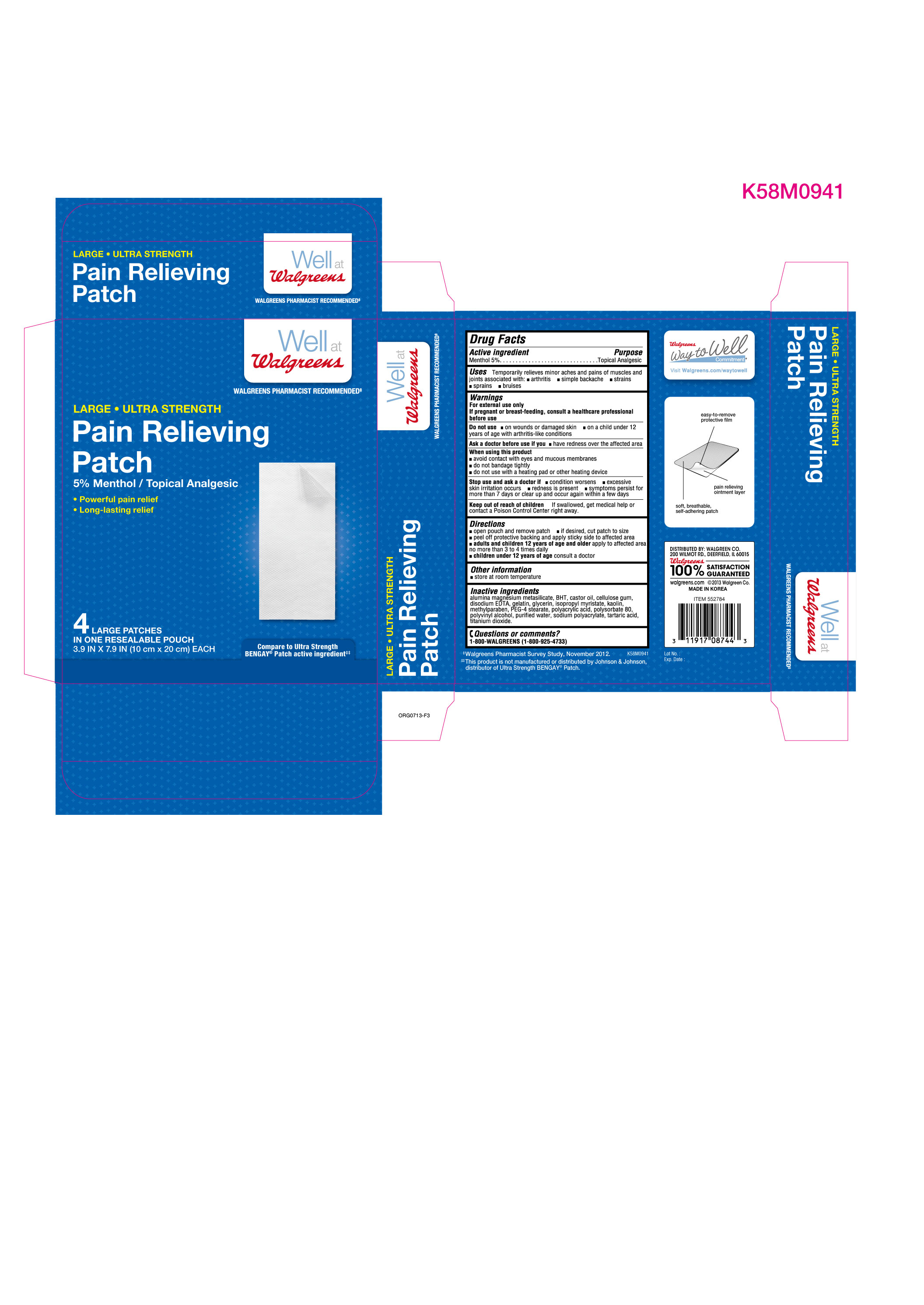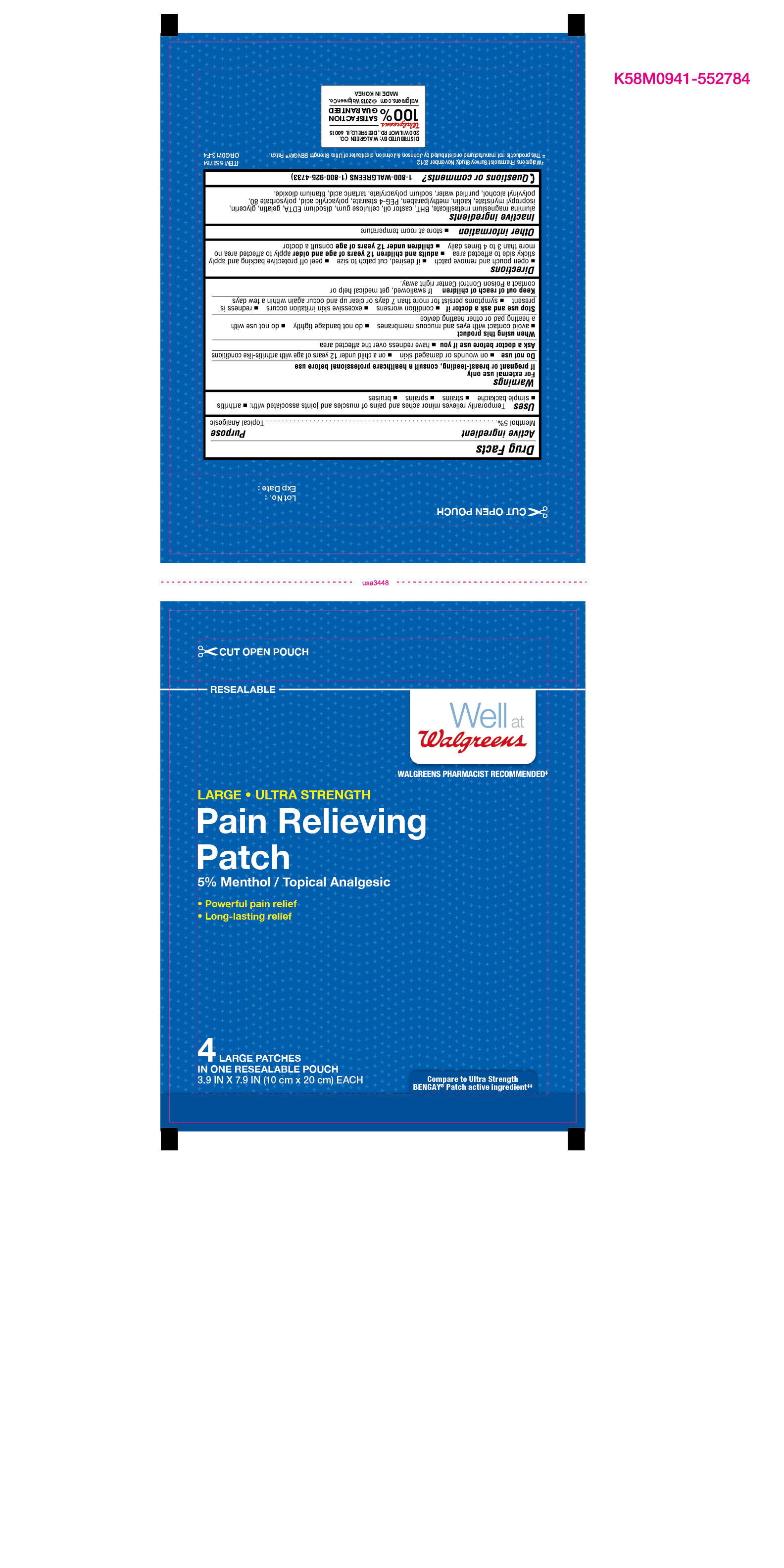 DRUG LABEL: Pain Relieving Patch
NDC: 0363-0151 | Form: PATCH
Manufacturer: Walgreen Co.
Category: otc | Type: HUMAN OTC DRUG LABEL
Date: 20131004

ACTIVE INGREDIENTS: Menthol .05 mg/1 g
INACTIVE INGREDIENTS: Silodrate; Butylated Hydroxytoluene; Castor Oil; Carboxymethylcellulose Sodium; Edetate Disodium; Gelatin; Glycerin; Isopropyl Myristate; Kaolin; Methylparaben; Peg-4 Stearate; Polysorbate 80; Polyvinyl Alcohol; Water; Tartaric Acid; Titanium Dioxide

Menthol 5% (Topical Analgesic)

Active Ingredient

Menthol 5%

Purpose

Topical Analgesic

Uses

Temporarily relieves minor aches and pains of muscles and joints associated with:

- arthritis
- simple backache
- strains
- sprains
- bruises

Warnings
For external use only
If pregnant or breast-feeding, consult a healthcare professional before use

Do not use

- on wounds or damaged skin
- on a child under 12 years of age with arthritis-like conditions

Ask a doctor before use if you

- have redness over the affected area

When using this product

- avoid contact with eyes and mucous membranes
- do not bandage tightly
- do not use with a heating pad or other heating devices

Stop use and ask a doctor if

- condition worsens
- excessive skin irritation occurs
- redness is present
- symptoms persist for more than 7 days or clear up and occur again within a few days

Keep out of reach of children

If swallowed, get medical help or contact a Poison Control Center right away.

Directions

- open pouch and remove patch
- if desired, cut patch to size
- peel off protective backing and apply sticky side to affected area
- adults and children 12 years of age and older apply to affected area no more than 3 to 4 times daily
- children under 12 years of age consult a doctor

Other information

- store at room temperature

Inactive ingredients

alumina magnesioum metasilicate, BHT, castor oil, cellulose gum, disodium EDTA, gelatin, glycerin, isopropyl myristate, kaolin, methylparaben, PEG-4 stearate, polyacrylic acid, polysorbate 80, polyvinyl alcohol, purified water, sodium polyacrylate, tartaric acid, titanium dioxide.

Questions or comments?

1-800-WALGREENS (1-800-925-4733)